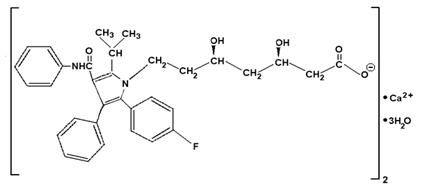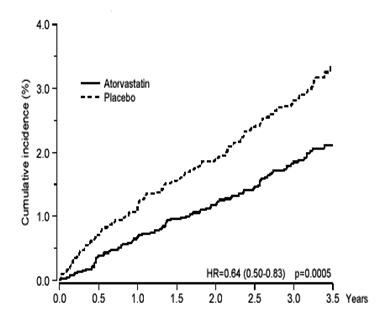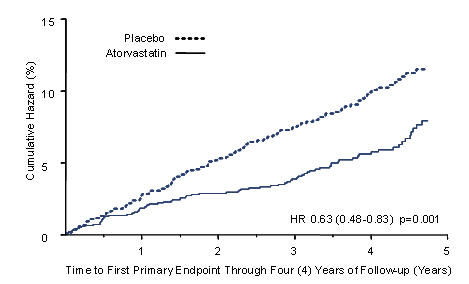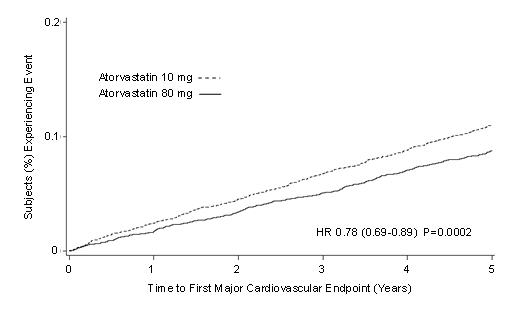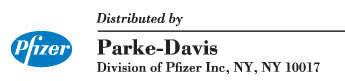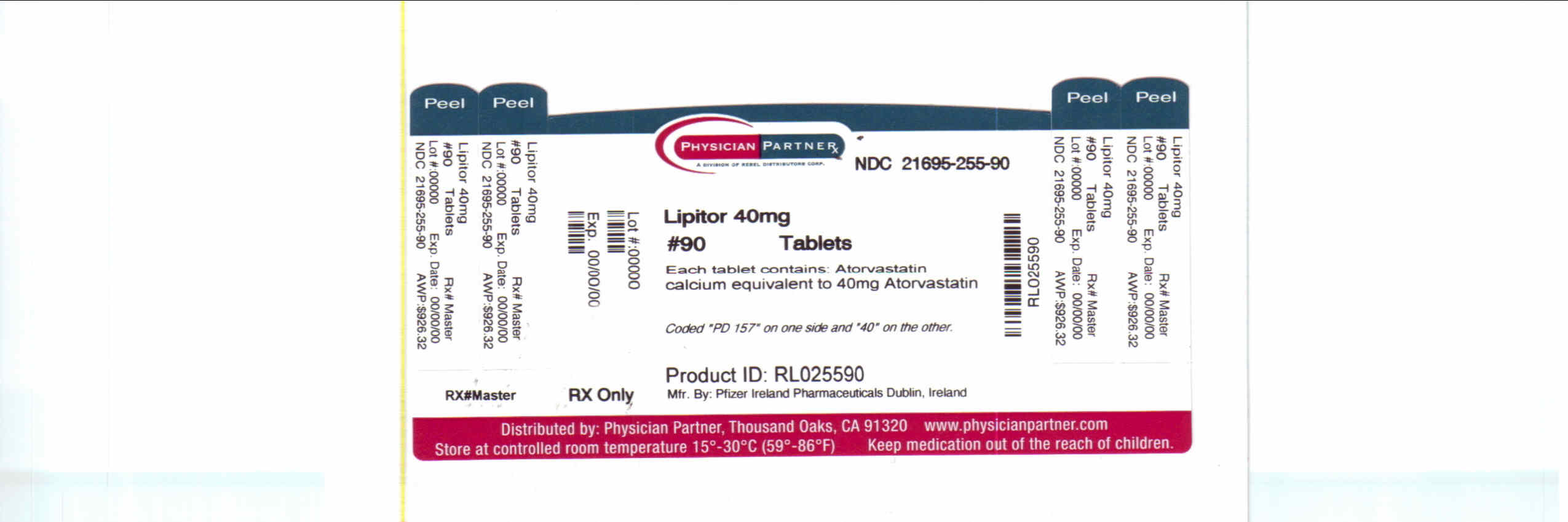 DRUG LABEL: Lipitor
NDC: 21695-255 | Form: TABLET, FILM COATED
Manufacturer: Rebel Distributors Corp
Category: prescription | Type: HUMAN PRESCRIPTION DRUG LABEL
Date: 20110103

ACTIVE INGREDIENTS: atorvastatin calcium 40 mg/1 1
INACTIVE INGREDIENTS: calcium carbonate; candelilla wax; croscarmellose sodium; hydroxypropyl cellulose; lactose monohydrate; magnesium stearate; cellulose, microcrystalline; HYPROMELLOSES; polyethylene glycol; talc; titanium dioxide; polysorbate 80

HIGHLIGHTS OF PRESCRIBING INFORMATION

These highlights do not include all the information needed to use LIPITOR safely and effectively. See full prescribing information for LIPITOR.
LIPITOR® (atorvastatin calcium) Tablets for oral administration
Initial U.S. Approval: 1996

1 INDICATIONS AND USAGE

LIPITOR is an inhibitor of HMG-CoA reductase (statin) indicated as an adjunct therapy to diet to:

- Reduce the risk of MI, stroke, revascularization procedures, and angina in patients without CHD, but with multiple risk factors (1.1).
- Reduce the risk of MI and stroke in patients with type 2 diabetes without CHD, but with multiple risk factors (1.1).
- Reduce the risk of non-fatal MI, fatal and non-fatal stroke, revascularization procedures, hospitalization for CHF, and angina in patients with CHD (1.1).
- Reduce elevated total-C, LDL-C, apo B, and TG levels and increase HDL-C in adult patients with primary hyperlipidemia (heterozygous familial and nonfamilial) and mixed dyslipidemia (1.2).
- Reduce elevated TG in patients with hypertriglyceridemia and primary dysbetalipoproteinemia (1.2).
- Reduce total-C and LDL-C in patients with homozygous familial hypercholesterolemia (HoFH) (1.2).
- Reduce elevated total-C, LDL-C, and apo B levels in boys and postmenarchal girls, 10 to 17 years of age, with heterozygous familial hypercholesterolemia after failing an adequate trial of diet therapy (1.2).

Limitations of Use

LIPITOR has not been studied in Fredrickson Types I and V dyslipidemias.

2 DOSAGE AND ADMINISTRATION

Dose range: 10 to 80 mg once daily (2.1).

Recommended start dose: 10 or 20 mg once daily (2.1).

Patients requiring large LDL-C reduction (>45%) may start at 40 mg once daily (2.1).

Pediatric starting dose: 10 mg once daily; maximum recommended dose: 20 mg once daily (2.2).

3 DOSAGE FORMS AND STRENGTHS

10, 20, 40, and 80 mg tablets (3).

4 CONTRAINDICATIONS

Active liver disease, which may include unexplained persistent elevations in hepatic transaminase levels (4.1).

Women who are pregnant or may become pregnant (4.3).

Nursing mothers (4.4).

Hypersensitivity to any component of this medication (4.2).

5 WARNINGS AND PRECAUTIONS

Skeletal muscle effects (e.g., myopathy and rhabdomyolysis): Risks increase when higher doses are used concomitantly with cyclosporine, fibrates, and strong CYP3A4 inhibitors (e.g., clarithromycin, itraconazole, HIV protease inhibitors). Predisposing factors include advanced age (> 65), uncontrolled hypothyroidism, and renal impairment. Rare cases of rhabdomyolysis with acute renal failure secondary to myoglobinuria have been reported. In cases of myopathy or rhabdomyolysis, therapy should be temporarily withheld or discontinued (5.1).

Liver enzyme abnormalities and monitoring: Persistent elevations in hepatic transaminases can occur. Monitor liver enzymes before and during treatment (5.2).

A higher incidence of hemorrhagic stroke was seen in patients without CHD but with stroke or TIA within the previous 6 months in the LIPITOR 80 mg group vs. placebo (5.5).

6 ADVERSE REACTIONS

The most commonly reported adverse reactions (incidence ≥ 2%) in patients treated with LIPITOR in placebo-controlled trials regardless of causality were: nasopharyngitis, arthralgia, diarrhea, pain in extremity, and urinary tract infection (6.1).

To report SUSPECTED ADVERSE REACTIONS, contact Pfizer at (1-800-438-1985 and www.pfizer.com) or FDA at 1-800-FDA-1088 or www.fda.gov/medwatch.

7 DRUG INTERACTIONS

Drug Interactions Associated with Increased Risk of Myopathy/Rhabdomyolysis (2.6, 5.1, 7, 12.3)
Interacting Agents | Prescribing Recommendations
Cyclosporine | Do not exceed 10 mg atorvastatin daily
Clarithromycin, itraconazole, HIV protease inhibitors (ritonavir plus saquinavir or lopinavir plus ritonavir) | Caution when exceeding doses > 20 mg atorvastatin daily. The lowest dose necessary should be used.

- Digoxin: Patients should be monitored appropriately (7.5).
- Oral Contraceptives: Values for norethindrone and ethinyl estradiol may be increased (7.6).
- Rifampin should be simultaneously co-administered with LIPITOR (7.4).

8 USE IN SPECIFIC POPULATIONS

- Hepatic impairment: Plasma concentrations markedly increased in patients with chronic alcoholic liver disease (12.3).

FULL PRESCRIBING INFORMATION

1 INDICATIONS AND USAGE

Therapy with lipid-altering agents should be only one component of multiple risk factor intervention in individuals at significantly increased risk for atherosclerotic vascular disease due to hypercholesterolemia. Drug therapy is recommended as an adjunct to diet when the response to a diet restricted in saturated fat and cholesterol and other nonpharmacologic measures alone has been inadequate. In patients with CHD or multiple risk factors for CHD, LIPITOR can be started simultaneously with diet.

1.1 Prevention of Cardiovascular Disease

In adult patients without clinically evident coronary heart disease, but with multiple risk factors for coronary heart disease such as age, smoking, hypertension, low HDL-C, or a family history of early coronary heart disease, LIPITOR is indicated to:

- Reduce the risk of myocardial infarction
- Reduce the risk of stroke
- Reduce the risk for revascularization procedures and angina

In patients with type 2 diabetes, and without clinically evident coronary heart disease, but with multiple risk factors for coronary heart disease such as retinopathy, albuminuria, smoking, or hypertension, LIPITOR is indicated to:

- Reduce the risk of myocardial infarction
- Reduce the risk of stroke

In patients with clinically evident coronary heart disease, LIPITOR is indicated to:

- Reduce the risk of non-fatal myocardial infarction
- Reduce the risk of fatal and non-fatal stroke
- Reduce the risk for revascularization procedures
- Reduce the risk of hospitalization for CHF
- Reduce the risk of angina

1.2 Hyperlipidemia

LIPITOR is indicated:

- As an adjunct to diet to reduce elevated total-C, LDL-C, apo B, and TG levels and to increase HDL-C in patients with primary hypercholesterolemia (heterozygous familial and nonfamilial) and mixed dyslipidemia (Fredrickson Types IIa and IIb);
- As an adjunct to diet for the treatment of patients with elevated serum TG levels (Fredrickson Type IV);
- For the treatment of patients with primary dysbetalipoproteinemia (Fredrickson Type III) who do not respond adequately to diet;
- To reduce total-C and LDL-C in patients with homozygous familial hypercholesterolemia as an adjunct to other lipid-lowering treatments (e.g., LDL apheresis) or if such treatments are unavailable;
- As an adjunct to diet to reduce total-C, LDL-C, and apo B levels in boys and postmenarchal girls, 10 to 17 years of age, with heterozygous familial hypercholesterolemia if after an adequate trial of diet therapy the following findings are present:
  1. LDL-C remains ≥ 190 mg/dL or
  2. LDL-C remains ≥ 160 mg/dL and:
    - there is a positive family history of premature cardiovascular disease or
    - two or more other CVD risk factors are present in the pediatric patient

1.3 Limitations of Use

LIPITOR has not been studied in conditions where the major lipoprotein abnormality is elevation of chylomicrons (Fredrickson Types I and V).

2 DOSAGE AND ADMINISTRATION

2.1 Hyperlipidemia (Heterozygous Familial and Nonfamilial) and Mixed Dyslipidemia (Fredrickson Types IIa and IIb)

The recommended starting dose of LIPITOR is 10 or 20 mg once daily. Patients who require a large reduction in LDL-C (more than 45%) may be started at 40 mg once daily. The dosage range of LIPITOR is 10 to 80 mg once daily. LIPITOR can be administered as a single dose at any time of the day, with or without food. The starting dose and maintenance doses of LIPITOR should be individualized according to patient characteristics such as goal of therapy and response (see current NCEP Guidelines). After initiation and/or upon titration of LIPITOR, lipid levels should be analyzed within 2 to 4 weeks and dosage adjusted accordingly.

2.2 Heterozygous Familial Hypercholesterolemia in Pediatric Patients (10–17 years of age)

The recommended starting dose of LIPITOR is 10 mg/day; the maximum recommended dose is 20 mg/day (doses greater than 20 mg have not been studied in this patient population). Doses should be individualized according to the recommended goal of therapy [see current NCEP Pediatric Panel Guidelines, Clinical Pharmacology (12), and Indications and Usage (1.2)]. Adjustments should be made at intervals of 4 weeks or more.

2.3 Homozygous Familial Hypercholesterolemia

The dosage of LIPITOR in patients with homozygous FH is 10 to 80 mg daily. LIPITOR should be used as an adjunct to other lipid-lowering treatments (e.g., LDL apheresis) in these patients or if such treatments are unavailable.

2.4 Concomitant Lipid-Lowering Therapy

LIPITOR may be used with bile acid resins. The combination of HMG-CoA reductase inhibitors (statins) and fibrates should generally be used with caution [see Warnings and Precautions, Skeletal Muscle (5.1), Drug Interactions (7)].

2.5 Dosage in Patients With Renal Impairment

Renal disease does not affect the plasma concentrations nor LDL-C reduction of LIPITOR; thus, dosage adjustment in patients with renal dysfunction is not necessary [see Warnings and Precautions, Skeletal Muscle (5.1), Clinical Pharmacology, Pharmacokinetics (12.3)].

2.6 Dosage in Patients Taking Cyclosporine, Clarithromycin, Itraconazole, or a Combination of Ritonavir plus Saquinavir or Lopinavir plus Ritonavir

In patients taking cyclosporine, therapy should be limited to LIPITOR 10 mg once daily. In patients taking clarithromycin, itraconazole, or in patients with HIV taking a combination of ritonavir plus saquinavir or lopinavir plus ritonavir, for doses of LIPITOR exceeding 20 mg, appropriate clinical assessment is recommended to ensure that the lowest dose necessary of LIPITOR is employed [see Warnings and Precautions, Skeletal Muscle (5.1), Drug Interactions (7)].

3 DOSAGE FORMS AND STRENGTHS

White, elliptical, film-coated tablets containing 10, 20, 40, and 80 mg atorvastatin calcium.

4 CONTRAINDICATIONS

4.3 Pregnancy

Women who are pregnant or may become pregnant. LIPITOR may cause fetal harm when administered to a pregnant woman. Serum cholesterol and triglycerides increase during normal pregnancy, and cholesterol or cholesterol derivatives are essential for fetal development. Atherosclerosis is a chronic process and discontinuation of lipid-lowering drugs during pregnancy should have little impact on the outcome of long-term therapy of primary hypercholesterolemia. There are no adequate and well-controlled studies of LIPITOR use during pregnancy; however in rare reports, congenital anomalies were observed following intrauterine exposure to statins. In rat and rabbit animal reproduction studies, atorvastatin revealed no evidence of teratogenicity. LIPITOR SHOULD BE ADMINISTERED TO WOMEN OF CHILDBEARING AGE ONLY WHEN SUCH PATIENTS ARE HIGHLY UNLIKELY TO CONCEIVE AND HAVE BEEN INFORMED OF THE POTENTIAL HAZARDS. If the patient becomes pregnant while taking this drug, LIPITOR should be discontinued immediately and the patient apprised of the potential hazard to the fetus [see Use in Specific Populations (8.1)].

4.4 Nursing mothers

It is not known whether atorvastatin is excreted into human milk; however a small amount of another drug in this class does pass into breast milk. Because statins have the potential for serious adverse reactions in nursing infants, women who require LIPITOR treatment should not breastfeed their infants [see Use in Specific Populations (8.3)].

5 WARNINGS AND PRECAUTIONS

5.1 Skeletal Muscle

Rare cases of rhabdomyolysis with acute renal failure secondary to myoglobinuria have been reported with LIPITOR and with other drugs in this class. A history of renal impairment may be a risk factor for the development of rhabdomyolysis. Such patients merit closer monitoring for skeletal muscle effects.

Atorvastatin, like other statins, occasionally causes myopathy, defined as muscle aches or muscle weakness in conjunction with increases in creatine phosphokinase (CPK) values >10 times ULN. The concomitant use of higher doses of atorvastatin with certain drugs such as cyclosporine and strong CYP3A4 inhibitors (e.g., clarithromycin, itraconazole, and HIV protease inhibitors) increases the risk of myopathy/rhabdomyolysis.

Myopathy should be considered in any patient with diffuse myalgias, muscle tenderness or weakness, and/or marked elevation of CPK. Patients should be advised to report promptly unexplained muscle pain, tenderness, or weakness, particularly if accompanied by malaise or fever. LIPITOR therapy should be discontinued if markedly elevated CPK levels occur or myopathy is diagnosed or suspected.

The risk of myopathy during treatment with drugs in this class is increased with concurrent administration of cyclosporine, fibric acid derivatives, erythromycin, clarithromycin, combination of ritonavir plus saquinavir or lopinavir plus ritonavir, niacin, or azole antifungals. Physicians considering combined therapy with LIPITOR and fibric acid derivatives, erythromycin, clarithromycin, a combination of ritonavir plus saquinavir or lopinavir plus ritonavir, immunosuppressive drugs, azole antifungals, or lipid-modifying doses of niacin should carefully weigh the potential benefits and risks and should carefully monitor patients for any signs or symptoms of muscle pain, tenderness, or weakness, particularly during the initial months of therapy and during any periods of upward dosage titration of either drug. Lower starting and maintenance doses of atorvastatin should be considered when taken concomitantly with the aforementioned drugs (see Drug Interactions (7)). Periodic creatine phosphokinase (CPK) determinations may be considered in such situations, but there is no assurance that such monitoring will prevent the occurrence of severe myopathy.

Prescribing recommendations for interacting agents are summarized in Table 1 [see also Dosage and Administration (2.6), Drug Interactions (7), Clinical Pharmacology (12.3)].

Table 1. Drug Interactions Associated with Increased Risk of Myopathy/Rhabdomyolysis
Interacting Agents | Prescribing Recommendations
Cyclosporine | Do not exceed 10 mg atorvastatin daily
Clarithromycin, itraconazole, HIV protease inhibitors (ritonavir plus saquinavir or lopinavir plus ritonavir) | Caution when exceeding doses > 20mg atorvastatin daily. The lowest dose necessary should be used.

LIPITOR therapy should be temporarily withheld or discontinued in any patient with an acute, serious condition suggestive of a myopathy or having a risk factor predisposing to the development of renal failure secondary to rhabdomyolysis (e.g., severe acute infection, hypotension, major surgery, trauma, severe metabolic, endocrine and electrolyte disorders, and uncontrolled seizures).

5.2 Liver Dysfunction

Statins, like some other lipid-lowering therapies, have been associated with biochemical abnormalities of liver function. Persistent elevations (>3 times the upper limit of normal [ULN] occurring on 2 or more occasions) in serum transaminases occurred in 0.7% of patients who received LIPITOR in clinical trials. The incidence of these abnormalities was 0.2%, 0.2%, 0.6%, and 2.3% for 10, 20, 40, and 80 mg, respectively.

One patient in clinical trials developed jaundice. Increases in liver function tests (LFT) in other patients were not associated with jaundice or other clinical signs or symptoms. Upon dose reduction, drug interruption, or discontinuation, transaminase levels returned to or near pretreatment levels without sequelae. Eighteen of 30 patients with persistent LFT elevations continued treatment with a reduced dose of LIPITOR.

It is recommended that liver function tests be performed prior to and at 12 weeks following both the initiation of therapy and any elevation of dose, and periodically (e.g., semiannually) thereafter. Liver enzyme changes generally occur in the first 3 months of treatment with LIPITOR. Patients who develop increased transaminase levels should be monitored until the abnormalities resolve. Should an increase in ALT or AST of >3 times ULN persist, reduction of dose or withdrawal of LIPITOR is recommended.

LIPITOR should be used with caution in patients who consume substantial quantities of alcohol and/or have a history of liver disease. Active liver disease or unexplained persistent transaminase elevations are contraindications to the use of LIPITOR [see Contraindications (4.1)].

5.3 Endocrine Function

Statins interfere with cholesterol synthesis and theoretically might blunt adrenal and/or gonadal steroid production. Clinical studies have shown that LIPITOR does not reduce basal plasma cortisol concentration or impair adrenal reserve. The effects of statins on male fertility have not been studied in adequate numbers of patients. The effects, if any, on the pituitary-gonadal axis in premenopausal women are unknown. Caution should be exercised if a statin is administered concomitantly with drugs that may decrease the levels or activity of endogenous steroid hormones, such as ketoconazole, spironolactone, and cimetidine.

5.4 CNS Toxicity

Brain hemorrhage was seen in a female dog treated for 3 months at 120 mg/kg/day. Brain hemorrhage and optic nerve vacuolation were seen in another female dog that was sacrificed in moribund condition after 11 weeks of escalating doses up to 280 mg/kg/day. The 120 mg/kg dose resulted in a systemic exposure approximately 16 times the human plasma area-under-the-curve (AUC, 0–24 hours) based on the maximum human dose of 80 mg/day. A single tonic convulsion was seen in each of 2 male dogs (one treated at 10 mg/kg/day and one at 120 mg/kg/day) in a 2-year study. No CNS lesions have been observed in mice after chronic treatment for up to 2 years at doses up to 400 mg/kg/day or in rats at doses up to 100 mg/kg/day. These doses were 6 to 11 times (mouse) and 8 to 16 times (rat) the human AUC (0–24) based on the maximum recommended human dose of 80 mg/day.

CNS vascular lesions, characterized by perivascular hemorrhages, edema, and mononuclear cell infiltration of perivascular spaces, have been observed in dogs treated with other members of this class. A chemically similar drug in this class produced optic nerve degeneration (Wallerian degeneration of retinogeniculate fibers) in clinically normal dogs in a dose-dependent fashion at a dose that produced plasma drug levels about 30 times higher than the mean drug level in humans taking the highest recommended dose.

5.5 Use in Patients with Recent Stroke or TIA

In a post-hoc analysis of the Stroke Prevention by Aggressive Reduction in Cholesterol Levels (SPARCL) study where LIPITOR 80 mg vs. placebo was administered in 4,731 subjects without CHD who had a stroke or TIA within the preceding 6 months, a higher incidence of hemorrhagic stroke was seen in the LIPITOR 80 mg group compared to placebo (55, 2.3% atorvastatin vs. 33, 1.4% placebo; HR: 1.68, 95% CI: 1.09, 2.59; p=0.0168). The incidence of fatal hemorrhagic stroke was similar across treatment groups (17 vs. 18 for the atorvastatin and placebo groups, respectively). The incidence of nonfatal hemorrhagic stroke was significantly higher in the atorvastatin group (38, 1.6%) as compared to the placebo group (16, 0.7%). Some baseline characteristics, including hemorrhagic and lacunar stroke on study entry, were associated with a higher incidence of hemorrhagic stroke in the atorvastatin group [see Adverse Reactions (6.1)].

6 ADVERSE REACTIONS

The following serious adverse reactions are discussed in greater detail in other sections of the label:

Rhabdomyolysis and myopathy [see Warnings and Precautions (5.1)]

Liver enzyme abnormalities [see Warnings and Precautions (5.2)]

6.1 Clinical Trial Adverse Experiences

Because clinical trials are conducted under widely varying conditions, the adverse reaction rates observed in the clinical studies of a drug cannot be directly compared to rates in the clinical trials of another drug and may not reflect the rates observed in clinical practice.

In the LIPITOR placebo-controlled clinical trial database of 16,066 patients (8755 LIPITOR vs. 7311 placebo; age range 10–93 years, 39% women, 91% Caucasians, 3% Blacks, 2% Asians, 4% other) with a median treatment duration of 53 weeks, 9.7% of patients on LIPITOR and 9.5% of the patients on placebo discontinued due to adverse reactions regardless of causality. The five most common adverse reactions in patients treated with LIPITOR that led to treatment discontinuation and occurred at a rate greater than placebo were: myalgia (0.7%), diarrhea (0.5%), nausea (0.4%), alanine aminotransferase increase (0.4%), and hepatic enzyme increase (0.4%).

The most commonly reported adverse reactions (incidence ≥ 2% and greater than placebo) regardless of causality, in patients treated with LIPITOR in placebo controlled trials (n=8755) were: nasopharyngitis (8.3%), arthralgia (6.9%), diarrhea (6.8%), pain in extremity (6.0%), and urinary tract infection (5.7%).

Table 2 summarizes the frequency of clinical adverse reactions, regardless of causality, reported in ≥ 2% and at a rate greater than placebo in patients treated with LIPITOR (n=8755), from seventeen placebo-controlled trials.

Table 2. Clinical adverse reactions occurring in ≥ 2% in patents treated with any dose of LIPITOR and at an incidence greater than placebo regardless of causality (% of patients).
Adverse Reaction [Adverse Reaction ≥ 2% in any dose greater than placebo] | Any dose N=8755 | 10 mg N=3908 | 20 mg N=188 | 40 mg N=604 | 80 mg N=4055 | Placebo N=7311
Nasopharyngitis | 8.3 | 12.9 | 5.3 | 7.0 | 4.2 | 8.2
Arthralgia | 6.9 | 8.9 | 11.7 | 10.6 | 4.3 | 6.5
Diarrhea | 6.8 | 7.3 | 6.4 | 14.1 | 5.2 | 6.3
Pain in extremity | 6.0 | 8.5 | 3.7 | 9.3 | 3.1 | 5.9
Urinary tract infection | 5.7 | 6.9 | 6.4 | 8.0 | 4.1 | 5.6
Dyspepsia | 4.7 | 5.9 | 3.2 | 6.0 | 3.3 | 4.3
Nausea | 4.0 | 3.7 | 3.7 | 7.1 | 3.8 | 3.5
Musculoskeletal pain | 3.8 | 5.2 | 3.2 | 5.1 | 2.3 | 3.6
Muscle Spasms | 3.6 | 4.6 | 4.8 | 5.1 | 2.4 | 3.0
Myalgia | 3.5 | 3.6 | 5.9 | 8.4 | 2.7 | 3.1
Insomnia | 3.0 | 2.8 | 1.1 | 5.3 | 2.8 | 2.9
Pharyngolaryngeal pain | 2.3 | 3.9 | 1.6 | 2.8 | 0.7 | 2.1

Other adverse reactions reported in placebo-controlled studies include:

Body as a whole: malaise, pyrexia; Digestive system: abdominal discomfort, eructation, flatulence, hepatitis, cholestasis; Musculoskeletal system: musculoskeletal pain, muscle fatigue, neck pain, joint swelling; Metabolic and nutritional system: transaminases increase, liver function test abnormal, blood alkaline phosphatase increase, creatine phosphokinase increase, hyperglycemia; Nervous system: nightmare; Respiratory system: epistaxis; Skin and appendages: urticaria; Special senses: vision blurred, tinnitus; Urogenital system: white blood cells urine positive.

Anglo-Scandinavian Cardiac Outcomes Trial (ASCOT)

In ASCOT [see Clinical Studies (14.1)] involving 10,305 participants (age range 40–80 years, 19% women; 94.6% Caucasians, 2.6% Africans, 1.5% South Asians, 1.3% mixed/other) treated with LIPITOR 10 mg daily (n=5,168) or placebo (n=5,137), the safety and tolerability profile of the group treated with LIPITOR was comparable to that of the group treated with placebo during a median of 3.3 years of follow-up.

Collaborative Atorvastatin Diabetes Study (CARDS)

In CARDS [see Clinical Studies (14.1)] involving 2,838 subjects (age range 39–77 years, 32% women; 94.3% Caucasians, 2.4% South Asians, 2.3% Afro-Caribbean, 1.0% other) with type 2 diabetes treated with LIPITOR 10 mg daily (n=1,428) or placebo (n=1,410), there was no difference in the overall frequency of adverse reactions or serious adverse reactions between the treatment groups during a median follow-up of 3.9 years. No cases of rhabdomyolysis were reported.

Treating to New Targets Study (TNT)

In TNT [see Clinical Studies (14.1)] involving 10,001 subjects (age range 29–78 years, 19% women; 94.1% Caucasians, 2.9% Blacks, 1.0% Asians, 2.0% other) with clinically evident CHD treated with LIPITOR 10 mg daily (n=5006) or LIPITOR 80 mg daily (n=4995), there were more serious adverse reactions and discontinuations due to adverse reactions in the high-dose atorvastatin group (92, 1.8%; 497, 9.9%, respectively) as compared to the low-dose group (69, 1.4%; 404, 8.1%, respectively) during a median follow-up of 4.9 years. Persistent transaminase elevations (≥3 × ULN twice within 4–10 days) occurred in 62 (1.3%) individuals with atorvastatin 80 mg and in nine (0.2%) individuals with atorvastatin 10 mg. Elevations of CK (≥ 10 × ULN) were low overall, but were higher in the high-dose atorvastatin treatment group (13, 0.3%) compared to the low-dose atorvastatin group (6, 0.1%).

Incremental Decrease in Endpoints through Aggressive Lipid Lowering Study (IDEAL)

In IDEAL [see Clinical Studies (14.1)] involving 8,888 subjects (age range 26–80 years, 19% women; 99.3% Caucasians, 0.4% Asians, 0.3% Blacks, 0.04% other) treated with LIPITOR 80 mg/day (n=4439) or simvastatin 20–40 mg daily (n=4449), there was no difference in the overall frequency of adverse reactions or serious adverse reactions between the treatment groups during a median follow-up of 4.8 years.

Stroke Prevention by Aggressive Reduction in Cholesterol Levels (SPARCL)

In SPARCL involving 4731 subjects (age range 21–92 years, 40% women; 93.3% Caucasians, 3.0% Blacks, 0.6% Asians, 3.1% other) without clinically evident CHD but with a stroke or transient ischemic attack (TIA) within the previous 6 months treated with LIPITOR 80 mg (n=2365) or placebo (n=2366) for a median follow-up of 4.9 years, there was a higher incidence of persistent hepatic transaminase elevations (≥ 3 × ULN twice within 4–10 days) in the atorvastatin group (0.9%) compared to placebo (0.1%). Elevations of CK (>10 × ULN) were rare, but were higher in the atorvastatin group (0.1%) compared to placebo (0.0%). Diabetes was reported as an adverse reaction in 144 subjects (6.1%) in the atorvastatin group and 89 subjects (3.8%) in the placebo group [see Warnings and Precautions (5.5)].

In a post-hoc analysis, LIPITOR 80 mg reduced the incidence of ischemic stroke (218/2365, 9.2% vs. 274/2366, 11.6%) and increased the incidence of hemorrhagic stroke (55/2365, 2.3% vs. 33/2366, 1.4%) compared to placebo. The incidence of fatal hemorrhagic stroke was similar between groups (17 LIPITOR vs. 18 placebo). The incidence of non-fatal hemorrhagic strokes was significantly greater in the atorvastatin group (38 non-fatal hemorrhagic strokes) as compared to the placebo group (16 non-fatal hemorrhagic strokes). Subjects who entered the study with a hemorrhagic stroke appeared to be at increased risk for hemorrhagic stroke [7 (16%) LIPITOR vs. 2 (4%) placebo].

There were no significant differences between the treatment groups for all-cause mortality: 216 (9.1%) in the LIPITOR 80 mg/day group vs. 211 (8.9%) in the placebo group. The proportions of subjects who experienced cardiovascular death were numerically smaller in the LIPITOR 80 mg group (3.3%) than in the placebo group (4.1%). The proportions of subjects who experienced non-cardiovascular death were numerically larger in the LIPITOR 80 mg group (5.0%) than in the placebo group (4.0%).

6.2 Postmarketing Experience

The following adverse reactions have been identified during postapproval use of LIPITOR. Because these reactions are reported voluntarily from a population of uncertain size, it is not always possible to reliably estimate their frequency or establish a causal relationship to drug exposure.

Adverse reactions associated with LIPITOR therapy reported since market introduction, that are not listed above, regardless of causality assessment, include the following: anaphylaxis, angioneurotic edema, bullous rashes (including erythema multiforme, Stevens-Johnson syndrome, and toxic epidermal necrolysis), rhabdomyolysis, fatigue, tendon rupture, hepatic failure, dizziness, memory impairment, depression, and peripheral neuropathy.

6.3 Pediatric Patients (ages 10–17 years)

In a 26-week controlled study in boys and postmenarchal girls (n=140, 31% female; 92% Caucasians, 1.6% Blacks, 1.6% Asians, 4.8% other), the safety and tolerability profile of LIPITOR 10 to 20 mg daily was generally similar to that of placebo [see Clinical Studies (14.6) and Use in Special Populations, Pediatric Use (8.4)].

7 DRUG INTERACTIONS

The risk of myopathy during treatment with statins is increased with concurrent administration of fibric acid derivatives, lipid-modifying doses of niacin, cyclosporine, or strong CYP 3A4 inhibitors (e.g., clarithromycin, HIV protease inhibitors, and itraconazole) [see Warnings and Precautions, Skeletal Muscle (5.1) and Clinical Pharmacology (12.3)].

7.1 Strong Inhibitors of CYP 3A4

LIPITOR is metabolized by cytochrome P450 3A4. Concomitant administration of LIPITOR with strong inhibitors of CYP 3A4 can lead to increases in plasma concentrations of atorvastatin. The extent of interaction and potentiation of effects depend on the variability of effect on CYP 3A4.

Clarithromycin: Atorvastatin AUC was significantly increased with concomitant administration of LIPITOR 80 mg with clarithromycin (500 mg twice daily) compared to that of LIPITOR alone [see Clinical Pharmacology (12.3)]. Therefore, in patients taking clarithromycin, caution should be used when the LIPITOR dose exceeds 20 mg [see Warnings and Precautions, Skeletal Muscle (5.1) and Dosage and Administration (2.6)].

Combination of Protease Inhibitors: Atorvastatin AUC was significantly increased with concomitant administration of LIPITOR 40 mg with ritonavir plus saquinavir (400 mg twice daily) or LIPITOR 20 mg with lopinavir plus ritonavir (400 mg + 100 mg twice daily) compared to that of LIPITOR alone [see Clinical Pharmacology (12.3)]. Therefore, in patients taking HIV protease inhibitors, caution should be used when the LIPITOR dose exceeds 20 mg [see Warnings and Precautions, Skeletal Muscle (5.1) and Dosage and Administration (2.6)].

Itraconazole: Atorvastatin AUC was significantly increased with concomitant administration of LIPITOR 40 mg and itraconazole 200 mg [see Clinical Pharmacology (12.3)]. Therefore, in patients taking itraconazole, caution should be used when the LIPITOR dose exceeds 20 mg [see Warnings and Precautions, Skeletal Muscle (5.1) and Dosage and Administration (2.6)].

7.2 Grapefruit Juice

Contains one or more components that inhibit CYP 3A4 and can increase plasma concentrations of atorvastatin, especially with excessive grapefruit juice consumption (>1.2 liters per day).

7.3 Cyclosporine

Atorvastatin and atorvastatin-metabolites are substrates of the OATP1B1 transporter. Inhibitors of the OATP1B1 (e.g., cyclosporine) can increase the bioavailability of atorvastatin. Atorvastatin AUC was significantly increased with concomitant administration of LIPITOR 10 mg and cyclosporine 5.2 mg/kg/day compared to that of LIPITOR alone [see Clinical Pharmacology (12.3)]. In cases where co-administration of LIPITOR with cyclosporine is necessary, the dose of LIPITOR should not exceed 10 mg [see Warnings and Precautions, Skeletal Muscle (5.1)].

7.4 Rifampin or other Inducers of Cytochrome P450 3A4

Concomitant administration of LIPITOR with inducers of cytochrome P450 3A4 (e.g., efavirenz, rifampin) can lead to variable reductions in plasma concentrations of atorvastatin. Due to the dual interaction mechanism of rifampin, simultaneous co-administration of LIPITOR with rifampin is recommended, as delayed administration of LIPITOR after administration of rifampin has been associated with a significant reduction in atorvastatin plasma concentrations.

7.5 Digoxin

When multiple doses of LIPITOR and digoxin were coadministered, steady state plasma digoxin concentrations increased by approximately 20%. Patients taking digoxin should be monitored appropriately.

7.6 Oral Contraceptives

Co-administration of LIPITOR and an oral contraceptive increased AUC values for norethindrone and ethinyl estradiol [see Clinical Pharmacology (12.3)]. These increases should be considered when selecting an oral contraceptive for a woman taking LIPITOR.

7.7 Warfarin

LIPITOR had no clinically significant effect on prothrombin time when administered to patients receiving chronic warfarin treatment.

8 USE IN SPECIFIC POPULATIONS

8.1 Pregnancy

TERATOGENIC EFFECTS

Pregnancy Category X

LIPITOR is contraindicated in women who are or may become pregnant. Serum cholesterol and triglycerides increase during normal pregnancy. Lipid lowering drugs offer no benefit during pregnancy because cholesterol and cholesterol derivatives are needed for normal fetal development. Atherosclerosis is a chronic process, and discontinuation of lipid-lowering drugs during pregnancy should have little impact on long-term outcomes of primary hypercholesterolemia therapy.

There are no adequate and well-controlled studies of atorvastatin use during pregnancy. There have been rare reports of congenital anomalies following intrauterine exposure to statins. In a review of about 100 prospectively followed pregnancies in women exposed to other statins, the incidences of congenital anomalies, spontaneous abortions, and fetal deaths/stillbirths did not exceed the rate expected in the general population. However, this study was only able to exclude a three-to-four-fold increased risk of congenital anomalies over background incidence. In 89% of these cases, drug treatment started before pregnancy and stopped during the first trimester when pregnancy was identified.

Atorvastatin crosses the rat placenta and reaches a level in fetal liver equivalent to that of maternal plasma. Atorvastatin was not teratogenic in rats at doses up to 300 mg/kg/day or in rabbits at doses up to 100 mg/kg/day. These doses resulted in multiples of about 30 times (rat) or 20 times (rabbit) the human exposure based on surface area (mg/m^2) [see Contraindications, Pregnancy (4.3)].

In a study in rats given 20, 100, or 225 mg/kg/day, from gestation day 7 through to lactation day 21 (weaning), there was decreased pup survival at birth, neonate, weaning, and maturity in pups of mothers dosed with 225 mg/kg/day. Body weight was decreased on days 4 and 21 in pups of mothers dosed at 100 mg/kg/day; pup body weight was decreased at birth and at days 4, 21, and 91 at 225 mg/kg/day. Pup development was delayed (rotorod performance at 100 mg/kg/day and acoustic startle at 225 mg/kg/day; pinnae detachment and eye-opening at 225 mg/kg/day). These doses correspond to 6 times (100 mg/kg) and 22 times (225 mg/kg) the human AUC at 80 mg/day.

Statins may cause fetal harm when administered to a pregnant woman. LIPITOR should be administered to women of childbearing potential only when such patients are highly unlikely to conceive and have been informed of the potential hazards. If the woman becomes pregnant while taking LIPITOR, it should be discontinued immediately and the patient advised again as to the potential hazards to the fetus and the lack of known clinical benefit with continued use during pregnancy.

8.3 Nursing Mothers

It is not known whether atorvastatin is excreted in human milk, but a small amount of another drug in this class does pass into breast milk. Nursing rat pups had plasma and liver drug levels of 50% and 40%, respectively, of that in their mother's milk. Animal breast milk drug levels may not accurately reflect human breast milk levels. Because another drug in this class passes into human milk and because statins have a potential to cause serious adverse reactions in nursing infants, women requiring LIPITOR treatment should be advised not to nurse their infants [seeContraindications (4)].

8.4 Pediatric Use

Safety and effectiveness in patients 10–17 years of age with heterozygous familial hypercholesterolemia have been evaluated in a controlled clinical trial of 6 months' duration in adolescent boys and postmenarchal girls. Patients treated with LIPITOR had an adverse experience profile generally similar to that of patients treated with placebo. The most common adverse experiences observed in both groups, regardless of causality assessment, were infections. Doses greater than 20 mg have not been studied in this patient population. In this limited controlled study, there was no significant effect on growth or sexual maturation in boys or on menstrual cycle length in girls [see Clinical Studies (14.6); Adverse Reactions, Pediatric Patients (ages 10–17 years) (6.3); and Dosage and Administration, Heterozygous Familial Hypercholesterolemia in Pediatric Patients (10–17 years of age) (2.2)]. Adolescent females should be counseled on appropriate contraceptive methods while on LIPITOR therapy [see Contraindications, Pregnancy (4.3) and Use in Specific Populations, Pregnancy (8.1)]. LIPITOR has not been studied in controlled clinical trials involving pre-pubertal patients or patients younger than 10 years of age.

Clinical efficacy with doses up to 80 mg/day for 1 year have been evaluated in an uncontrolled study of patients with homozygous FH including 8 pediatric patients [see Clinical Studies, Homozygous Familial Hypercholesterolemia (14.5) ].

8.5 Geriatric Use

Of the 39,828 patients who received LIPITOR in clinical studies, 15,813 (40%) were ≥65 years old and 2,800 (7%) were ≥75 years old. No overall differences in safety or effectiveness were observed between these subjects and younger subjects, and other reported clinical experience has not identified differences in responses between the elderly and younger patients, but greater sensitivity of some older adults cannot be ruled out. Since advanced age (≥65 years) is a predisposing factor for myopathy, LIPITOR should be prescribed with caution in the elderly.

8.6 Hepatic Impairment

Lipitor is contraindicated in patients with active liver disease which may include unexplained persistent elevations in hepatic transaminase levels [see Contraindications (4) and Pharmacokinetics (12.3)].

10 OVERDOSAGE

There is no specific treatment for LIPITOR overdosage. In the event of an overdose, the patient should be treated symptomatically, and supportive measures instituted as required. Due to extensive drug binding to plasma proteins, hemodialysis is not expected to significantly enhance LIPITOR clearance.

11 DESCRIPTION

LIPITOR is a synthetic lipid-lowering agent. Atorvastatin is an inhibitor of 3-hydroxy-3-methylglutaryl-coenzyme A (HMG-CoA) reductase. This enzyme catalyzes the conversion of HMG-CoA to mevalonate, an early and rate-limiting step in cholesterol biosynthesis.

Atorvastatin calcium is [R-(R*, R*)]-2-(4-fluorophenyl)-ß, δ-dihydroxy-5-(1-methylethyl)-3-phenyl-4-[(phenylamino)carbonyl]-1H-pyrrole-1-heptanoic acid, calcium salt (2:1) trihydrate. The empirical formula of atorvastatin calcium is (C33H34 FN2O5)2Ca•3H2O and its molecular weight is 1209.42. Its structural formula is:

Atorvastatin calcium is a white to off-white crystalline powder that is insoluble in aqueous solutions of pH 4 and below. Atorvastatin calcium is very slightly soluble in distilled water, pH 7.4 phosphate buffer, and acetonitrile; slightly soluble in ethanol; and freely soluble in methanol.

LIPITOR Tablets for oral administration contain 10, 20, 40, or 80 mg atorvastatin and the following inactive ingredients: calcium carbonate, USP; candelilla wax, FCC; croscarmellose sodium, NF; hydroxypropyl cellulose, NF; lactose monohydrate, NF; magnesium stearate, NF; microcrystalline cellulose, NF; Opadry White YS-1-7040 (hypromellose, polyethylene glycol, talc, titanium dioxide); polysorbate 80, NF; simethicone emulsion.

12 CLINICAL PHARMACOLOGY

12.1 Mechanism of Action

LIPITOR is a selective, competitive inhibitor of HMG-CoA reductase, the rate-limiting enzyme that converts 3-hydroxy-3-methylglutaryl-coenzyme A to mevalonate, a precursor of sterols, including cholesterol. Cholesterol and triglycerides circulate in the bloodstream as part of lipoprotein complexes. With ultracentrifugation, these complexes separate into HDL (high-density lipoprotein), IDL (intermediate-density lipoprotein), LDL (low-density lipoprotein), and VLDL (very-low-density lipoprotein) fractions. Triglycerides (TG) and cholesterol in the liver are incorporated into VLDL and released into the plasma for delivery to peripheral tissues. LDL is formed from VLDL and is catabolized primarily through the high-affinity LDL receptor. Clinical and pathologic studies show that elevated plasma levels of total cholesterol (total-C), LDL-cholesterol (LDL-C), and apolipoprotein B (apo B) promote human atherosclerosis and are risk factors for developing cardiovascular disease, while increased levels of HDL-C are associated with a decreased cardiovascular risk.

In animal models, LIPITOR lowers plasma cholesterol and lipoprotein levels by inhibiting HMG-CoA reductase and cholesterol synthesis in the liver and by increasing the number of hepatic LDL receptors on the cell surface to enhance uptake and catabolism of LDL; LIPITOR also reduces LDL production and the number of LDL particles. LIPITOR reduces LDL-C in some patients with homozygous familial hypercholesterolemia (FH), a population that rarely responds to other lipid-lowering medication(s).

A variety of clinical studies have demonstrated that elevated levels of total-C, LDL-C, and apo B (a membrane complex for LDL-C) promote human atherosclerosis. Similarly, decreased levels of HDL-C (and its transport complex, apo A) are associated with the development of atherosclerosis. Epidemiologic investigations have established that cardiovascular morbidity and mortality vary directly with the level of total-C and LDL-C, and inversely with the level of HDL-C.

LIPITOR reduces total-C, LDL-C, and apo B in patients with homozygous and heterozygous FH, nonfamilial forms of hypercholesterolemia, and mixed dyslipidemia. LIPITOR also reduces VLDL-C and TG and produces variable increases in HDL-C and apolipoprotein A-1. LIPITOR reduces total-C, LDL-C, VLDL-C, apo B, TG, and non-HDL-C, and increases HDL-C in patients with isolated hypertriglyceridemia. LIPITOR reduces intermediate density lipoprotein cholesterol (IDL-C) in patients with dysbetalipoproteinemia.

Like LDL, cholesterol-enriched triglyceride-rich lipoproteins, including VLDL, intermediate density lipoprotein (IDL), and remnants, can also promote atherosclerosis. Elevated plasma triglycerides are frequently found in a triad with low HDL-C levels and small LDL particles, as well as in association with non-lipid metabolic risk factors for coronary heart disease. As such, total plasma TG has not consistently been shown to be an independent risk factor for CHD. Furthermore, the independent effect of raising HDL or lowering TG on the risk of coronary and cardiovascular morbidity and mortality has not been determined.

12.2 Pharmacodynamics

LIPITOR, as well as some of its metabolites, are pharmacologically active in humans. The liver is the primary site of action and the principal site of cholesterol synthesis and LDL clearance. Drug dosage, rather than systemic drug concentration, correlates better with LDL-C reduction. Individualization of drug dosage should be based on therapeutic response [see Dosage and Administration (2)].

12.3 Pharmacokinetics

Absorption: LIPITOR is rapidly absorbed after oral administration; maximum plasma concentrations occur within 1 to 2 hours. Extent of absorption increases in proportion to LIPITOR dose. The absolute bioavailability of atorvastatin (parent drug) is approximately 14% and the systemic availability of HMG-CoA reductase inhibitory activity is approximately 30%. The low systemic availability is attributed to presystemic clearance in gastrointestinal mucosa and/or hepatic first-pass metabolism. Although food decreases the rate and extent of drug absorption by approximately 25% and 9%, respectively, as assessed by Cmax and AUC, LDL-C reduction is similar whether LIPITOR is given with or without food. Plasma LIPITOR concentrations are lower (approximately 30% for Cmax and AUC) following evening drug administration compared with morning. However, LDL-C reduction is the same regardless of the time of day of drug administration [see Dosage and Administration (2)].

Distribution: Mean volume of distribution of LIPITOR is approximately 381 liters. LIPITOR is ≥98% bound to plasma proteins. A blood/plasma ratio of approximately 0.25 indicates poor drug penetration into red blood cells. Based on observations in rats, LIPITOR is likely to be secreted in human milk [see Contraindications, Nursing Mothers (4.4) and Use in Specific Populations, Nursing Mothers (8.3)].

Metabolism: LIPITOR is extensively metabolized to ortho- and parahydroxylated derivatives and various beta-oxidation products. In vitro inhibition of HMG-CoA reductase by ortho- and parahydroxylated metabolites is equivalent to that of LIPITOR. Approximately 70% of circulating inhibitory activity for HMG-CoA reductase is attributed to active metabolites. In vitro studies suggest the importance of LIPITOR metabolism by cytochrome P450 3A4, consistent with increased plasma concentrations of LIPITOR in humans following co-administration with erythromycin, a known inhibitor of this isozyme [see Drug Interactions (7.1)]. In animals, the ortho-hydroxy metabolite undergoes further glucuronidation.

Excretion: LIPITOR and its metabolites are eliminated primarily in bile following hepatic and/or extra-hepatic metabolism; however, the drug does not appear to undergo enterohepatic recirculation. Mean plasma elimination half-life of LIPITOR in humans is approximately 14 hours, but the half-life of inhibitory activity for HMG-CoA reductase is 20 to 30 hours due to the contribution of active metabolites. Less than 2% of a dose of LIPITOR is recovered in urine following oral administration.

Specific Populations

Geriatric: Plasma concentrations of LIPITOR are higher (approximately 40% for Cmax and 30% for AUC) in healthy elderly subjects (age ≥65 years) than in young adults. Clinical data suggest a greater degree of LDL-lowering at any dose of drug in the elderly patient population compared to younger adults [see Use in Specific Populations, Geriatric Use (8.5)].

Pediatric: Pharmacokinetic data in the pediatric population are not available.

Gender: Plasma concentrations of LIPITOR in women differ from those in men (approximately 20% higher for Cmax and 10% lower for AUC); however, there is no clinically significant difference in LDL-C reduction with LIPITOR between men and women.

Renal Impairment: Renal disease has no influence on the plasma concentrations or LDL-C reduction of LIPITOR; thus, dose adjustment in patients with renal dysfunction is not necessary [see Dosage and Administration, Dosage in Patients with Renal Impairment (2.5), Warnings and Precautions, Skeletal Muscle (5.1) ].

Hemodialysis: While studies have not been conducted in patients with end-stage renal disease, hemodialysis is not expected to significantly enhance clearance of LIPITOR since the drug is extensively bound to plasma proteins.

Hepatic Impairment: In patients with chronic alcoholic liver disease, plasma concentrations of LIPITOR are markedly increased. Cmax and AUC are each 4-fold greater in patients with Childs-Pugh A disease. Cmax and AUC are approximately 16-fold and 11-fold increased, respectively, in patients with Childs-Pugh B disease [see Contraindications (4.1)].

TABLE 3. Effect of Co-administered Drugs on the Pharmacokinetics of Atorvastatin
Co-administered drug and dosing regimen | Atorvastatin
 | Dose (mg) | Change in AUC [Data given as x-fold change represent a simple ratio between co-administration and atorvastatin alone (i.e., 1-fold = no change). Data given as % change represent % difference relative to atorvastatin alone (i.e., 0% = no change).] | Change in Cmax
[See Sections 5.1 and 7 for clinical significance.] Cyclosporine 5.2 mg/kg/day, stable dose | 10 mg QD for 28 days | ↑ 8.7 fold | ↑10.7 fold
Lopinavir 400 mg BID/ ritonavir 100 mg BID, 14 days | 20 mg QD for 4 days | ↑ 5.9 fold | ↑ 4.7 fold
Ritonavir 400 mg BID/ saquinavir 400mg BID, 15 days | 40 mg QD for 4 days | ↑ 3.9 fold | ↑ 4.3 fold
Clarithromycin 500 mg BID, 9 days | 80 mg QD for 8 days | ↑ 4.4 fold | ↑ 5.4 fold
Itraconazole 200 mg QD, 4 days | 40 mg SD | ↑ 3.3 fold | ↑ 20%
Grapefruit Juice, 240 mL QD [Greater increases in AUC (up to 2.5 fold) and/or Cmax (up to 71%) have been reported with excessive grapefruit consumption (≥ 750 mL – 1.2 liters per day).] | 40 mg, SD | ↑ 37% | ↑ 16%
Diltiazem 240 mg QD, 28 days | 40 mg, SD | ↑ 51% | No change
Erythromycin 500 mg QID, 7 days | 10 mg, SD | ↑ 33% | ↑ 38%
Amlodipine 10 mg, single dose | 80 mg, SD | ↑ 15% | ↓ 12 %
Cimetidine 300 mg QD, 4 weeks | 10 mg QD for 2 weeks | ↓ Less than 1% | ↓ 11%
Colestipol 10 mg BID, 28 weeks | 40 mg QD for 28 weeks | Not determined | ↓ 26% [Single sample taken 8–16 h post dose.]
Maalox TC® 30 mL QD, 17 days | 10 mg QD for 15 days | ↓ 33% | ↓ 34%
Efavirenz 600 mg QD, 14 days | 10 mg for 3 days | ↓ 41% | ↓ 1%
Rifampin 600 mg QD, 7 days (co-administered) [Due to the dual interaction mechanism of rifampin, simultaneous co-administration of atorvastatin with rifampin is recommended, as delayed administration of atorvastatin after administration of rifampin has been associated with a significant reduction in atorvastatin plasma concentrations.] | 40 mg SD | ↑ 30% | ↑ 2.7 fold
Rifampin 600 mg QD, 5 days (doses separated) | 40 mg SD | ↓ 80% | ↓ 40%
Gemfibrozil 600mg BID, 7 days | 40mg SD | ↑ 35% | ↓ Less than 1%
Fenofibrate 160mg QD, 7 days | 40mg SD | ↑ 3% | ↑ 2%

TABLE 4. Effect of Atorvastatin on the Pharmacokinetics of Co-administered Drugs
Atorvastatin | Co-administered drug and dosing regimen
 | Drug/Dose (mg) | Change in AUC | Change in Cmax
80 mg QD for 15 days | Antipyrine, 600 mg SD | ↑ 3% | ↓ 11%
80 mg QD for 14 days | [See Section 7 for clinical significance.] Digoxin 0.25 mg QD, 20 days | ↑ 15% | ↑ 20 %
40 mg QD for 22 days | Oral contraceptive QD, 2 months - norethindrone 1mg - ethinyl estradiol 35µg | ↑ 28% ↑ 19% | ↑ 23% ↑ 30%

13 NONCLINICAL TOXICOLOGY

13.1 Carcinogenesis, Mutagenesis, Impairment of Fertility

In a 2-year carcinogenicity study in rats at dose levels of 10, 30, and 100 mg/kg/day, 2 rare tumors were found in muscle in high-dose females: in one, there was a rhabdomyosarcoma and, in another, there was a fibrosarcoma. This dose represents a plasma AUC (0–24) value of approximately 16 times the mean human plasma drug exposure after an 80 mg oral dose.

A 2-year carcinogenicity study in mice given 100, 200, or 400 mg/kg/day resulted in a significant increase in liver adenomas in high-dose males and liver carcinomas in high-dose females. These findings occurred at plasma AUC (0–24) values of approximately 6 times the mean human plasma drug exposure after an 80 mg oral dose.

In vitro, atorvastatin was not mutagenic or clastogenic in the following tests with and without metabolic activation: the Ames test with Salmonella typhimurium and Escherichia coli, the HGPRT forward mutation assay in Chinese hamster lung cells, and the chromosomal aberration assay in Chinese hamster lung cells. Atorvastatin was negative in the in vivo mouse micronucleus test.

Studies in rats performed at doses up to 175 mg/kg (15 times the human exposure) produced no changes in fertility. There was aplasia and aspermia in the epididymis of 2 of 10 rats treated with 100 mg/kg/day of atorvastatin for 3 months (16 times the human AUC at the 80 mg dose); testis weights were significantly lower at 30 and 100 mg/kg and epididymal weight was lower at 100 mg/kg. Male rats given 100 mg/kg/day for 11 weeks prior to mating had decreased sperm motility, spermatid head concentration, and increased abnormal sperm. Atorvastatin caused no adverse effects on semen parameters, or reproductive organ histopathology in dogs given doses of 10, 40, or 120 mg/kg for two years.

14 CLINICAL STUDIES

14.1 Prevention of Cardiovascular Disease

In the Anglo-Scandinavian Cardiac Outcomes Trial (ASCOT), the effect of LIPITOR on fatal and non-fatal coronary heart disease was assessed in 10,305 hypertensive patients 40–80 years of age (mean of 63 years), without a previous myocardial infarction and with TC levels ≤251 mg/dL (6.5 mmol/L). Additionally, all patients had at least 3 of the following cardiovascular risk factors: male gender (81.1%), age >55 years (84.5%), smoking (33.2%), diabetes (24.3%), history of CHD in a first-degree relative (26%), TC:HDL >6 (14.3%), peripheral vascular disease (5.1%), left ventricular hypertrophy (14.4%), prior cerebrovascular event (9.8%), specific ECG abnormality (14.3%), proteinuria/albuminuria (62.4%). In this double-blind, placebo-controlled study, patients were treated with anti-hypertensive therapy (Goal BP <140/90 mm Hg for non-diabetic patients; <130/80 mm Hg for diabetic patients) and allocated to either LIPITOR 10 mg daily (n=5168) or placebo (n=5137), using a covariate adaptive method which took into account the distribution of nine baseline characteristics of patients already enrolled and minimized the imbalance of those characteristics across the groups. Patients were followed for a median duration of 3.3 years.

The effect of 10 mg/day of LIPITOR on lipid levels was similar to that seen in previous clinical trials.

LIPITOR significantly reduced the rate of coronary events [either fatal coronary heart disease (46 events in the placebo group vs. 40 events in the LIPITOR group) or non-fatal MI (108 events in the placebo group vs. 60 events in the LIPITOR group)] with a relative risk reduction of 36% [(based on incidences of 1.9% for LIPITOR vs. 3.0% for placebo), p=0.0005 (see Figure 1)]. The risk reduction was consistent regardless of age, smoking status, obesity, or presence of renal dysfunction. The effect of LIPITOR was seen regardless of baseline LDL levels. Due to the small number of events, results for women were inconclusive.

Figure 1: Effect of LIPITOR 10 mg/day on Cumulative Incidence of Non-Fatal Myocardial Infarction or Coronary Heart Disease Death (in ASCOT-LLA)

LIPITOR also significantly decreased the relative risk for revascularization procedures by 42%. Although the reduction of fatal and non-fatal strokes did not reach a pre-defined significance level (p=0.01), a favorable trend was observed with a 26% relative risk reduction (incidences of 1.7% for LIPITOR and 2.3% for placebo). There was no significant difference between the treatment groups for death due to cardiovascular causes (p=0.51) or noncardiovascular causes (p=0.17).

In the Collaborative Atorvastatin Diabetes Study (CARDS), the effect of LIPITOR on cardiovascular disease (CVD) endpoints was assessed in 2838 subjects (94% white, 68% male), ages 40–75 with type 2 diabetes based on WHO criteria, without prior history of cardiovascular disease and with LDL ≤ 160 mg/dL and TG ≤ 600 mg/dL. In addition to diabetes, subjects had 1 or more of the following risk factors: current smoking (23%), hypertension (80%), retinopathy (30%), or microalbuminuria (9%) or macroalbuminuria (3%). No subjects on hemodialysis were enrolled in the study. In this multicenter, placebo-controlled, double-blind clinical trial, subjects were randomly allocated to either LIPITOR 10 mg daily (1429) or placebo (1411) in a 1:1 ratio and were followed for a median duration of 3.9 years. The primary endpoint was the occurrence of any of the major cardiovascular events: myocardial infarction, acute CHD death, unstable angina, coronary revascularization, or stroke. The primary analysis was the time to first occurrence of the primary endpoint.

Baseline characteristics of subjects were: mean age of 62 years, mean HbA1c 7.7%; median LDL-C 120 mg/dL; median TC 207 mg/dL; median TG 151 mg/dL; median HDL-C 52 mg/dL.

The effect of LIPITOR 10 mg/day on lipid levels was similar to that seen in previous clinical trials.

LIPITOR significantly reduced the rate of major cardiovascular events (primary endpoint events) (83 events in the LIPITOR group vs. 127 events in the placebo group) with a relative risk reduction of 37%, HR 0.63, 95% CI (0.48, 0.83) (p=0.001) (see Figure 2). An effect of LIPITOR was seen regardless of age, sex, or baseline lipid levels.

LIPITOR significantly reduced the risk of stroke by 48% (21 events in the LIPITOR group vs. 39 events in the placebo group), HR 0.52, 95% CI (0.31, 0.89) (p=0.016) and reduced the risk of MI by 42% (38 events in the LIPITOR group vs. 64 events in the placebo group), HR 0.58, 95.1% CI (0.39, 0.86) (p=0.007). There was no significant difference between the treatment groups for angina, revascularization procedures, and acute CHD death.

There were 61 deaths in the LIPITOR group vs. 82 deaths in the placebo group (HR 0.73, p=0.059).

Figure 2: Effect of LIPITOR 10 mg/day on Time to Occurrence of Major Cardiovascular Event (myocardial infarction, acute CHD death, unstable angina, coronary revascularization, or stroke) in CARDS

In the Treating to New Targets Study (TNT), the effect of LIPITOR 80 mg/day vs. LIPITOR 10 mg/day on the reduction in cardiovascular events was assessed in 10,001 subjects (94% white, 81% male, 38% ≥65 years) with clinically evident coronary heart disease who had achieved a target LDL-C level <130 mg/dL after completing an 8-week, open-label, run-in period with LIPITOR 10 mg/day. Subjects were randomly assigned to either 10 mg/day or 80 mg/day of LIPITOR and followed for a median duration of 4.9 years. The primary endpoint was the time-to-first occurrence of any of the following major cardiovascular events (MCVE): death due to CHD, non-fatal myocardial infarction, resuscitated cardiac arrest, and fatal and non-fatal stroke. The mean LDL-C, TC, TG, non-HDL, and HDL cholesterol levels at 12 weeks were 73, 145, 128, 98, and 47 mg/dL during treatment with 80 mg of LIPITOR and 99, 177, 152, 129, and 48 mg/dL during treatment with 10 mg of LIPITOR.

Treatment with LIPITOR 80 mg/day significantly reduced the rate of MCVE (434 events in the 80 mg/day group vs. 548 events in the 10 mg/day group) with a relative risk reduction of 22%, HR 0.78, 95% CI (0.69, 0.89), p=0.0002 (see Figure 3 and Table 5). The overall risk reduction was consistent regardless of age (<65, ≥65) or gender.

Figure 3: Effect of LIPITOR 80 mg/day vs. 10 mg/day on Time to Occurrence of Major Cardiovascular Events (TNT)

TABLE 5. Overview of Efficacy Results in TNT
Endpoint | Atorvastatin 10 mg (N=5006) |  | Atorvastatin 80 mg (N=4995) |  | HR [Atorvastatin 80 mg: atorvastatin 10 mg] (95%CI)
PRIMARY ENDPOINT | n | (%) | n | (%)
First major cardiovascular endpoint | 548 | (10.9) | 434 | (8.7) | 0.78 (0.69, 0.89)
Components of the Primary Endpoint
CHD death | 127 | (2.5) | 101 | (2.0) | 0.80 (0.61, 1.03)
Non-fatal, non-procedure related MI | 308 | (6.2) | 243 | (4.9) | 0.78 (0.66, 0.93)
Resuscitated cardiac arrest | 26 | (0.5) | 25 | (0.5) | 0.96 (0.56, 1.67)
Stroke (fatal and non-fatal) | 155 | (3.1) | 117 | (2.3) | 0.75 (0.59, 0.96)
SECONDARY ENDPOINTS [Secondary endpoints not included in primary endpoint]
First CHF with hospitalization | 164 | (3.3) | 122 | (2.4) | 0.74 (0.59, 0.94)
First PVD endpoint | 282 | (5.6) | 275 | (5.5) | 0.97 (0.83, 1.15)
First CABG or other coronary revascularization procedure [Component of other secondary endpoints] | 904 | (18.1) | 667 | (13.4) | 0.72 (0.65, 0.80)
First documented angina endpoint | 615 | (12.3) | 545 | (10.9) | 0.88 (0.79, 0.99)
All-cause mortality | 282 | (5.6) | 284 | (5.7) | 1.01 (0.85, 1.19)
Components of All-Cause Mortality
Cardiovascular death | 155 | (3.1) | 126 | (2.5) | 0.81 (0.64, 1.03)
Noncardiovascular death | 127 | (2.5) | 158 | (3.2) | 1.25 (0.99, 1.57)
Cancer death | 75 | (1.5) | 85 | (1.7) | 1.13 (0.83, 1.55)
Other non-CV death | 43 | (0.9) | 58 | (1.2) | 1.35 (0.91, 2.00)
Suicide, homicide, and other traumatic non-CV death | 9 | (0.2) | 15 | (0.3) | 1.67 (0.73, 3.82)
HR=hazard ratio; CHD=coronary heart disease; CI=confidence interval; MI=myocardial infarction; CHF=congestive heart failure; CV=cardiovascular; PVD=peripheral vascular disease; CABG=coronary artery bypass graft
Confidence intervals for the Secondary Endpoints were not adjusted for multiple comparisons

Of the events that comprised the primary efficacy endpoint, treatment with LIPITOR 80 mg/day significantly reduced the rate of non-fatal, non-procedure related MI and fatal and non-fatal stroke, but not CHD death or resuscitated cardiac arrest (Table 5). Of the predefined secondary endpoints, treatment with LIPITOR 80 mg/day significantly reduced the rate of coronary revascularization, angina, and hospitalization for heart failure, but not peripheral vascular disease. The reduction in the rate of CHF with hospitalization was only observed in the 8% of patients with a prior history of CHF.

There was no significant difference between the treatment groups for all-cause mortality (Table 5). The proportions of subjects who experienced cardiovascular death, including the components of CHD death and fatal stroke, were numerically smaller in the LIPITOR 80 mg group than in the LIPITOR 10 mg treatment group. The proportions of subjects who experienced noncardiovascular death were numerically larger in the LIPITOR 80 mg group than in the LIPITOR 10 mg treatment group.

In the Incremental Decrease in Endpoints Through Aggressive Lipid Lowering Study (IDEAL), treatment with LIPITOR 80 mg/day was compared to treatment with simvastatin 20–40 mg/day in 8,888 subjects up to 80 years of age with a history of CHD to assess whether reduction in CV risk could be achieved. Patients were mainly male (81%), white (99%) with an average age of 61.7 years, and an average LDL-C of 121.5 mg/dL at randomization; 76% were on statin therapy. In this prospective, randomized, open-label, blinded endpoint (PROBE) trial with no run-in period, subjects were followed for a median duration of 4.8 years. The mean LDL-C, TC, TG, HDL, and non-HDL cholesterol levels at Week 12 were 78, 145, 115, 45, and 100 mg/dL during treatment with 80 mg of LIPITOR and 105, 179, 142, 47, and 132 mg/dL during treatment with 20–40 mg of simvastatin.

There was no significant difference between the treatment groups for the primary endpoint, the rate of first major coronary event (fatal CHD, non-fatal MI, and resuscitated cardiac arrest): 411 (9.3%) in the LIPITOR 80 mg/day group vs. 463 (10.4%) in the simvastatin 20–40 mg/day group, HR 0.89, 95% CI (0.78, 1.01), p=0.07.

There were no significant differences between the treatment groups for all-cause mortality: 366 (8.2%) in the LIPITOR 80 mg/day group vs. 374 (8.4%) in the simvastatin 20–40 mg/day group. The proportions of subjects who experienced CV or non-CV death were similar for the LIPITOR 80 mg group and the simvastatin 20–40 mg group.

14.2 Hyperlipidemia (Heterozygous Familial and Nonfamilial) and Mixed Dyslipidemia (Fredrickson Types IIa and IIb)

LIPITOR reduces total-C, LDL-C, VLDL-C, apo B, and TG, and increases HDL-C in patients with hyperlipidemia and mixed dyslipidemia. Therapeutic response is seen within 2 weeks, and maximum response is usually achieved within 4 weeks and maintained during chronic therapy.

LIPITOR is effective in a wide variety of patient populations with hyperlipidemia, with and without hypertriglyceridemia, in men and women, and in the elderly.

In two multicenter, placebo-controlled, dose-response studies in patients with hyperlipidemia, LIPITOR given as a single dose over 6 weeks, significantly reduced total-C, LDL-C, apo B, and TG. (Pooled results are provided in Table 6.)

TABLE 6. Dose Response in Patients With Primary Hyperlipidemia (Adjusted Mean % Change From Baseline) [Results are pooled from 2 dose-response studies.]
Dose | N | TC | LDL-C | Apo B | TG | HDL-C | Non-HDL-C/ HDL-C
Placebo | 21 | 4 | 4 | 3 | 10 | -3 | 7
10 | 22 | -29 | -39 | -32 | -19 | 6 | -34
20 | 20 | -33 | -43 | -35 | -26 | 9 | -41
40 | 21 | -37 | -50 | -42 | -29 | 6 | -45
80 | 23 | -45 | -60 | -50 | -37 | 5 | -53

In patients with Fredrickson Types IIa and IIb hyperlipoproteinemia pooled from 24 controlled trials, the median (25th and 75th percentile) percent changes from baseline in HDL-C for LIPITOR 10, 20, 40, and 80 mg were 6.4 (-1.4, 14), 8.7 (0, 17), 7.8 (0, 16), and 5.1 (-2.7, 15), respectively. Additionally, analysis of the pooled data demonstrated consistent and significant decreases in total-C, LDL-C, TG, total-C/HDL-C, and LDL-C/HDL-C.

In three multicenter, double-blind studies in patients with hyperlipidemia, LIPITOR was compared to other statins. After randomization, patients were treated for 16 weeks with either LIPITOR 10 mg per day or a fixed dose of the comparative agent (Table 7).

TABLE 7. Mean Percentage Change From Baseline at Endpoint (Double-Blind, Randomized, Active-Controlled Trials)
Treatment (Daily Dose) | N | Total-C | LDL-C | Apo B | TG | HDL-C | Non-HDL-C/ HDL-C
Study 1
LIPITOR 10 mg | 707 | -27 [Significantly different from lovastatin, ANCOVA, p ≤0.05] | -36 | -28 | -17 | +7 | -37
Lovastatin 20 mg | 191 | -19 | -27 | -20 | -6 | +7 | -28
95% CI for Diff [A negative value for the 95% CI for the difference between treatments favors LIPITOR for all except HDL-C, for which a positive value favors LIPITOR. If the range does not include 0, this indicates a statistically significant difference.] |  | -9.2, -6.5 | -10.7, -7.1 | -10.0, -6.5 | -15.2, -7.1 | -1.7, 2.0 | -11.1, -7.1
Study 2
LIPITOR 10 mg | 222 | -25 [Significantly different from pravastatin, ANCOVA, p ≤0.05] | -35 | -27 | -17 | +6 | -36
Pravastatin 20 mg | 77 | -17 | -23 | -17 | -9 | +8 | -28
95% CI for Diff |  | -10.8, -6.1 | -14.5, -8.2 | -13.4, -7.4 | -14.1, -0.7 | -4.9, 1.6 | -11.5, -4.1
Study 3
LIPITOR 10 mg | 132 | -29 [Significantly different from simvastatin, ANCOVA, p ≤0.05] | -37 | -34 | -23 | +7 | -39
Simvastatin 10 mg | 45 | -24 | -30 | -30 | -15 | +7 | -33
95% CI for Diff |  | -8.7, -2.7 | -10.1, -2.6 | -8.0, -1.1 | -15.1, -0.7 | -4.3, 3.9 | -9.6, -1.9

The impact on clinical outcomes of the differences in lipid-altering effects between treatments shown in Table 7 is not known. Table 7 does not contain data comparing the effects of LIPITOR 10 mg and higher doses of lovastatin, pravastatin, and simvastatin. The drugs compared in the studies summarized in the table are not necessarily interchangeable.

14.3 Hypertriglyceridemia (Fredrickson Type IV)

The response to LIPITOR in 64 patients with isolated hypertriglyceridemia treated across several clinical trials is shown in the table below (Table 8). For the LIPITOR-treated patients, median (min, max) baseline TG level was 565 (267–1502).

TABLE 8. Combined Patients With Isolated Elevated TG: Median (min, max) Percentage Change From Baseline
 | Placebo (N=12) | LIPITOR 10 mg (N=37) | LIPITOR 20 mg (N=13) | LIPITOR 80 mg (N=14)
Triglycerides | -12.4 (-36.6, 82.7) | -41.0 (-76.2, 49.4) | -38.7 (-62.7, 29.5) | -51.8 (-82.8, 41.3)
Total-C | -2.3 (-15.5, 24.4) | -28.2 (-44.9, -6.8) | -34.9 (-49.6, -15.2) | -44.4 (-63.5, -3.8)
LDL-C | 3.6 (-31.3, 31.6) | -26.5 (-57.7, 9.8) | -30.4 (-53.9, 0.3) | -40.5 (-60.6, -13.8)
HDL-C | 3.8 (-18.6, 13.4) | 13.8 (-9.7, 61.5) | 11.0 (-3.2, 25.2) | 7.5 (-10.8, 37.2)
VLDL-C | -1.0 (-31.9, 53.2) | -48.8 (-85.8, 57.3) | -44.6 (-62.2, -10.8) | -62.0 (-88.2, 37.6)
non-HDL-C | -2.8 (-17.6, 30.0) | -33.0 (-52.1, -13.3) | -42.7 (-53.7, -17.4) | -51.5 (-72.9, -4.3)

14.4 Dysbetalipoproteinemia (Fredrickson Type III)

The results of an open-label crossover study of 16 patients (genotypes: 14 apo E2/E2 and 2 apo E3/E2) with dysbetalipoproteinemia (Fredrickson Type III) are shown in the table below (Table 9).

TABLE 9. Open-Label Crossover Study of 16 Patients With Dysbetalipoproteinemia (Fredrickson Type III)
 |  | Median % Change (min, max)
 | Median (min, max) at Baseline (mg/dL) | LIPITOR 10 mg | LIPITOR 80 mg
Total-C | 442 (225, 1320) | -37 (-85, 17) | -58 (-90, -31)
Triglycerides | 678 (273, 5990) | -39 (-92, -8) | -53 (-95, -30)
IDL-C + VLDL-C | 215 (111, 613) | -32 (-76, 9) | -63 (-90, -8)
non-HDL-C | 411 (218, 1272) | -43 (-87, -19) | -64 (-92, -36)

14.5 Homozygous Familial Hypercholesterolemia

In a study without a concurrent control group, 29 patients ages 6 to 37 years with homozygous FH received maximum daily doses of 20 to 80 mg of LIPITOR. The mean LDL-C reduction in this study was 18%. Twenty-five patients with a reduction in LDL-C had a mean response of 20% (range of 7% to 53%, median of 24%); the remaining 4 patients had 7% to 24% increases in LDL-C. Five of the 29 patients had absent LDL-receptor function. Of these, 2 patients also had a portacaval shunt and had no significant reduction in LDL-C. The remaining 3 receptor-negative patients had a mean LDL-C reduction of 22%.

14.6 Heterozygous Familial Hypercholesterolemia in Pediatric Patients

In a double-blind, placebo-controlled study followed by an open-label phase, 187 boys and postmenarchal girls 10–17 years of age (mean age 14.1 years) with heterozygous familial hypercholesterolemia (FH) or severe hypercholesterolemia, were randomized to LIPITOR (n=140) or placebo (n=47) for 26 weeks and then all received LIPITOR for 26 weeks. Inclusion in the study required 1) a baseline LDL-C level ≥ 190 mg/dL or 2) a baseline LDL-C level ≥ 160 mg/dL and positive family history of FH or documented premature cardiovascular disease in a first or second-degree relative. The mean baseline LDL-C value was 218.6 mg/dL (range: 138.5–385.0 mg/dL) in the LIPITOR group compared to 230.0 mg/dL (range: 160.0–324.5 mg/dL) in the placebo group. The dosage of LIPITOR (once daily) was 10 mg for the first 4 weeks and uptitrated to 20 mg if the LDL-C level was > 130 mg/dL. The number of LIPITOR-treated patients who required uptitration to 20 mg after Week 4 during the double-blind phase was 80 (57.1%).

LIPITOR significantly decreased plasma levels of total-C, LDL-C, triglycerides, and apolipoprotein B during the 26-week double-blind phase (see Table 10).

TABLE 10. Lipid-altering Effects of LIPITOR in Adolescent Boys and Girls with Heterozygous Familial Hypercholesterolemia or Severe Hypercholesterolemia (Mean Percentage Change From Baseline at Endpoint in Intention-to-Treat Population)
DOSAGE | N | Total-C | LDL-C | HDL-C | TG | Apolipoprotein B
Placebo | 47 | -1.5 | -0.4 | -1.9 | 1.0 | 0.7
LIPITOR | 140 | -31.4 | -39.6 | 2.8 | -12.0 | -34.0

The mean achieved LDL-C value was 130.7 mg/dL (range: 70.0–242.0 mg/dL) in the LIPITOR group compared to 228.5 mg/dL (range: 152.0–385.0 mg/dL) in the placebo group during the 26-week double-blind phase.

The safety and efficacy of doses above 20 mg have not been studied in controlled trials in children. The long-term efficacy of LIPITOR therapy in childhood to reduce morbidity and mortality in adulthood has not been established.

15 REFERENCES

- [1]National Cholesterol Education Program (NCEP): Highlights of the Report of the Expert Panel on Blood Cholesterol Levels in Children and Adolescents, Pediatrics. 89(3):495–501. 1992.

16 HOW SUPPLIED/STORAGE AND HANDLING

40 mg tablets: coded "PD 157" on one side and "40" on the other.

NDC 21695-245-90 bottles of 90

Storage

Store at controlled room temperature 20 – 25°C (68 – 77°F) [see USP].

17 PATIENT COUNSELING INFORMATION

Patients taking LIPITOR should be advised that cholesterol is a chronic condition and they should adhere to their medication along with their National Cholesterol Education Program (NCEP)-recommended diet, a regular exercise program as appropriate, and periodic testing of a fasting lipid panel to determine goal attainment.

Patients should be advised about substances they should not take concomitantly with atorvastatin [see Warnings and Precautions (5.1)]. Patients should also be advised to inform other healthcare professionals prescribing a new medication that they are taking LIPITOR.

17.1 Muscle Pain

All patients starting therapy with LIPITOR should be advised of the risk of myopathy and told to report promptly any unexplained muscle pain, tenderness, or weakness. The risk of this occurring is increased when taking certain types of medication or consuming larger quantities (>1 liter) of grapefruit juice. They should discuss all medication, both prescription and over the counter, with their healthcare professional.

17.2 Liver Enzymes

It is recommended that liver function tests be performed prior to and at 12 weeks following both the initiation of therapy and any elevation of dose, and periodically (e.g., semiannually) thereafter.

17.3 Pregnancy

Women of childbearing age should be advised to use an effective method of birth control to prevent pregnancy while using LIPITOR. Discuss future pregnancy plans with your patients, and discuss when to stop LIPITOR if they are trying to conceive. Patients should be advised that if they become pregnant, they should stop taking LIPITOR and call their healthcare professional.

17.4 Breastfeeding

Women who are breastfeeding should be advised to not use LIPITOR. Patients who have a lipid disorder and are breastfeeding, should be advised to discuss the options with their healthcare professional.

Rx Only

Manufactured by:
Pfizer Ireland Pharmaceuticals
Dublin, Ireland

LAB-0021-24.0
June 2009

PATIENT INFORMATION

LIPITOR®
atorvastatin calcium
tablets

(LIP-ih-tore)

Read the Patient Information that comes with LIPITOR before you start taking it and each time you get a refill. There may be new information. This leaflet does not take the place of talking with your doctor about your condition or treatment.

If you have any questions about LIPITOR, ask your doctor or pharmacist.

What is LIPITOR?

LIPITOR is a prescription medicine that lowers cholesterol in your blood. It lowers the LDL-C ("bad" cholesterol) and triglycerides in your blood. It can raise your HDL-C ("good" cholesterol) as well. LIPITOR is for adults and children over 10 whose cholesterol does not come down enough with exercise and a low-fat diet alone.

LIPITOR can lower the risk for heart attack, stroke, certain types of heart surgery, and chest pain in patients who have heart disease or risk factors for heart disease such as:

- age, smoking, high blood pressure, low HDL-C, heart disease in the family.

LIPITOR can lower the risk for heart attack or stroke in patients with diabetes and risk factors such as:

- eye problems, kidney problems, smoking, or high blood pressure.

LIPITOR starts to work in about 2 weeks.

What is Cholesterol?

Cholesterol and triglycerides are fats that are made in your body. They are also found in foods. You need some cholesterol for good health, but too much is not good for you. Cholesterol and triglycerides can clog your blood vessels. It is especially important to lower your cholesterol if you have heart disease, smoke, have diabetes or high blood pressure, are older, or if heart disease starts early in your family.

Who Should Not Take LIPITOR?

Do not take LIPITOR if you:

- are pregnant or think you may be pregnant, or are planning to become pregnant. Lipitor may harm your unborn baby. If you get pregnant, stop taking LIPITOR and call your doctor right away.
- are breast feeding. LIPITOR can pass into your breast milk and may harm your baby.
- have liver problems.
- are allergic to LIPITOR or any of its ingredients. The active ingredient is atorvastatin. See the end of this leaflet for a complete list of ingredients in LIPITOR.

LIPITOR has not been studied in children under 10 years of age.

Before You Start LIPITOR

Tell your doctor if you:

- have muscle aches or weakness
- drink more than 2 glasses of alcohol daily
- have diabetes
- have a thyroid problem
- have kidney problems

Some medicines should not be taken with LIPITOR. Tell your doctor about all the medicines you take, including prescription and non-prescription medicines, vitamins, and herbal supplements. LIPITOR and certain other medicines can interact causing serious side effects. Especially tell your doctor if you take medicines for:

- your immune system
- cholesterol
- infections
- birth control
- heart failure
- HIV or AIDS

Know all the medicines you take. Keep a list of them with you to show your doctor and pharmacist.

How Should I Take LIPITOR?

- Take LIPITOR exactly as prescribed by your doctor. Do not change your dose or stop LIPITOR without talking to your doctor. Your doctor may do blood tests to check your cholesterol levels during your treatment with LIPITOR. Your dose of LIPITOR may be changed based on these blood test results.
- Take LIPITOR each day at any time of day at about the same time each day. LIPITOR can be taken with or without food.
  Don't break LIPITOR tablets before taking.
- Your doctor should start you on a low-fat diet before giving you LIPITOR. Stay on this low-fat diet when you take LIPITOR.
- If you miss a dose of LIPITOR, take it as soon as you remember. Do not take LIPITOR if it has been more than 12 hours since you missed your last dose. Wait and take the next dose at your regular time. Do not take 2 doses of LIPITOR at the same time.
- If you take too much LIPITOR or overdose, call your doctor or Poison Control Center right away. Or go to the nearest emergency room.

What Should I Avoid While Taking LIPITOR?

- Talk to your doctor before you start any new medicines. This includes prescription and non-prescription medicines, vitamins, and herbal supplements. LIPITOR and certain other medicines can interact causing serious side effects.
- Do not get pregnant. If you get pregnant, stop taking LIPITOR right away and call your doctor.

What are the Possible Side Effects of LIPITOR?

LIPITOR can cause serious side effects. These side effects have happened only to a small number of people. Your doctor can monitor you for them. These side effects usually go away if your dose is lowered or LIPITOR is stopped. These serious side effects include:

- Muscle problems. LIPITOR can cause serious muscle problems that can lead to kidney problems, including kidney failure. You have a higher chance for muscle problems if you are taking certain other medicines with LIPITOR.
- Liver problems. LIPITOR can cause liver problems. Your doctor may do blood tests to check your liver before you start taking LIPITOR, and while you take it.

Call your doctor right away if you have:

- muscle problems like weakness, tenderness, or pain that happen without a good reason, especially if you also have a fever or feel more tired than usual.
- allergic reactions including swelling of the face, lips, tongue, and/or throat that may cause difficulty in breathing or swallowing which may require treatment right away.
- nausea and vomiting.
- passing brown or dark-colored urine.
- you feel more tired than usual
- your skin and whites of your eyes get yellow.
- stomach pain.
- allergic skin reactions.

In clinical studies, patients reported the following common side effects while taking LIPITOR: diarrhea, upset stomach, muscle and joint pain, and alterations in some laboratory blood tests.

The following additional side effects have been reported with LIPITOR:

tiredness, and tendon problems.

Talk to your doctor or pharmacist if you have side effects that bother you or that will not go away.

These are not all the side effects of LIPITOR. Ask your doctor or pharmacist for a complete list.

How do I store LIPITOR

- Store LIPITOR at room temperature, 68 to 77°F (20 to 25°C).
- Do not keep medicine that is out of date or that you no longer need.
- Keep LIPITOR and all medicines out of the reach of children. Be sure that if you throw medicine away, it is out of the reach of children.

General Information About LIPITOR

Medicines are sometimes prescribed for conditions that are not mentioned in patient information leaflets. Do not use LIPITOR for a condition for which it was not prescribed. Do not give LIPITOR to other people, even if they have the same problem you have. It may harm them.

This leaflet summarizes the most important information about LIPITOR. If you would like more information, talk with your doctor. You can ask your doctor or pharmacist for information about LIPITOR that is written for health professionals. Or you can go to the LIPITOR website at www.lipitor.com.

What are the Ingredients in LIPITOR?

Active Ingredient: atorvastatin calcium

Inactive Ingredients: calcium carbonate, USP; candelilla wax, FCC; croscarmellose sodium, NF; hydroxypropyl cellulose, NF; lactose monohydrate, NF; magnesium stearate, NF; microcrystalline cellulose, NF; Opadry White YS-1-7040 (hypromellose, polyethylene glycol, talc, titanium dioxide); polysorbate 80, NF; simethicone emulsion.

Rx Only

Manufactured by Pfizer Ireland Pharmaceuticals
Dublin, Ireland

LAB-0348-4.0 June 2009

Repackaged by:

Rebel Distributors Corp

Thousand Oaks, CA 91320